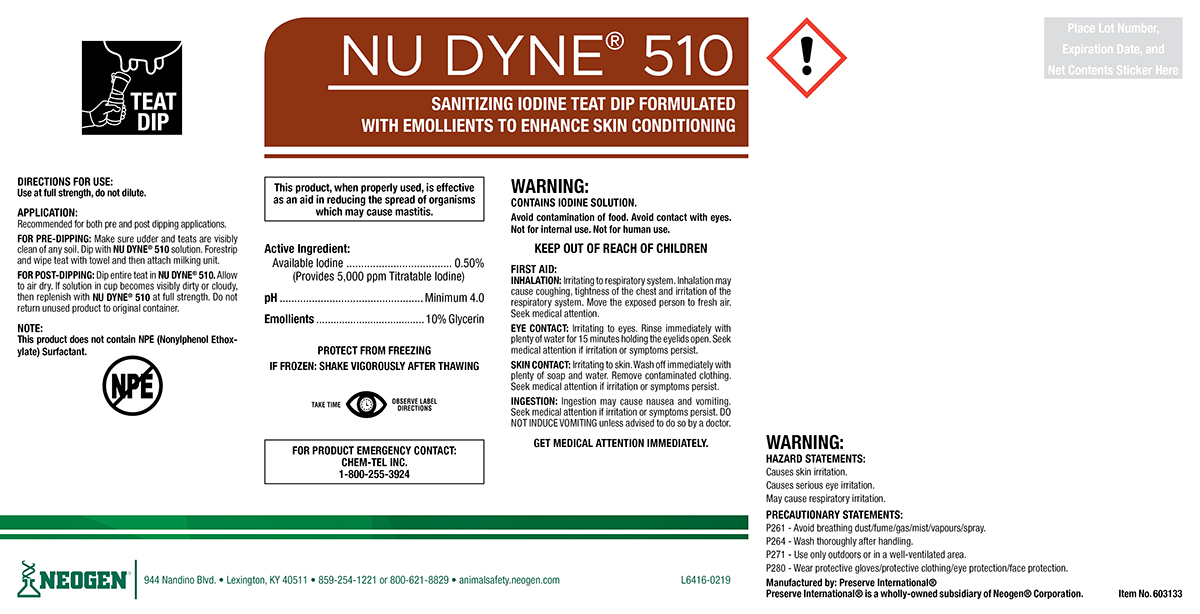 DRUG LABEL: NU DYNE 510
NDC: 60648-9005 | Form: SOLUTION
Manufacturer: Preserve International
Category: animal | Type: OTC ANIMAL DRUG LABEL
Date: 20190516

ACTIVE INGREDIENTS: IODINE 5.09 g/1 L; GLYCERIN 100.29 g/1 L

NU-Dyne® 510

DIRECTIONS FOR USE:

Use at full strength, do not dilute.

APPLICATION:

Recommended for both pre and post dipping applications.

FOR PRE-DIPPING: Make sure udder and teats are visibly clean of any soil. Dip with NU DYNE® 510 solution. Forestrip and wipe teat with towel and then attach milking unit.

FOR POST-DIPPING: Dip Entire teat in NU DYNE® 510. Allow to air dry. If solution in cup becomes visibly dirty or cloudy, then replenish with NU-DYNE® 510 at full strength. Do not return unused product to original container.

NOTE:

This product does not contain NPE (Nonylphenol Ethoxylate) Surfactant.

WARNINGS AND PRECAUTIONS

PROTECT FROM FREEZING

IF FROZEN: SHAKE VIGOROUSLY AFTER THAWING

WARNINGS AND PRECAUTIONS

TAKE TIME OBSERVE LABEL DIRECTIONS

WARNING:

CONTAINS IODINE SOLUTION.

Avoid contamination of food. Avoid contact with eyes. Not for internal use. Not for human use.

KEEP OUT OF REACH OF CHILDREN

FIRST AID:

INHALATION: Irritating to respiratory system. Inhalation may cause coughing, tightness of the chest and irritation of the respiratory system. Move the exposed person to fresh air. Seek medical attention.

EYECONTACT: Irritating to the eyes. Rinse immediately with plenty of water for 15 minutes holding te eyelids open. Seek medical attention if irritation or symptoms persist.

SKIN CONTACT: Irritating to skin. Wash off immediately with plenty of soap and water. Remove contaminated clothing. Seek medical attention if irritation or symptoms persist.

INGESTION: Ingestion may cause nausea and vomiting. Seek medical attention if irritation or symptoms persist. DO NOT INDUCE VOMITING unless advised to do so by a doctor.
GET MEDICAL ATTENTION IMMEDIATELY.

FOR PRODUCT EMERGENCY CONTACT: Chem-Tel Inc. 1-800-255-3924

HAZARD STATEMENTS:

Causes skin irritation.

Causes serious eye irritation.

May cause respiratory irritation.

PRECAUSTIONARY STATEMENTS:

P261 - Avoid breathing dust/fume/gas/mist/vapours/spray.

P264 - Wash thoroughly after handling.

P271 - Use only outdoors or in a well-ventilated area.

P280 - Wear protective gloves/protective clothing/eye protection/face protection.

PACKAGE LABEL

NU-DYNE® 510

SANITIZING IODINE TEAT DIP FORMULATED WITH
EMOLLIENTS TO ENHANCE SKIN CONDITIONING

This product, when properly used, is effective as an aid
in reducing the spread of organisms which may cause
mastitis.

Active Ingredient..........0.50% Available Iodine (provides 5,000 ppm titratable iodine)
pH.....................................Minimum 4.0
Emollients........................10% Glycerin

Manufactured By: Preserve International®

Preserve International® is a wholly-owned subsidiary of Neogen® Corporation.

NEOGEN®

944 Nandino Blvd.

Lexington, KY 40511

859-254-1221 or 800-621-8829

animalsafety.neogen.com